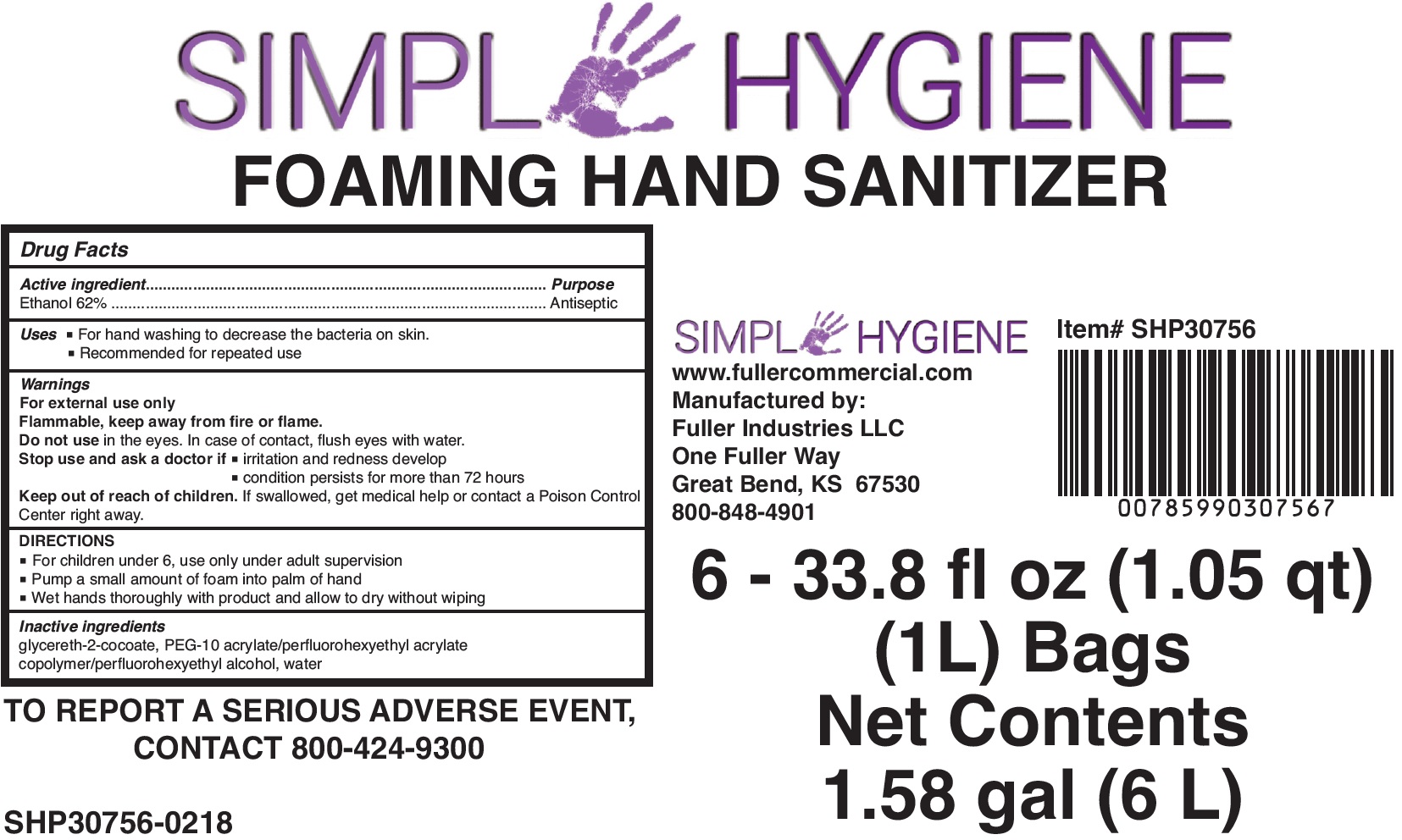 DRUG LABEL: Simple Hygiene Hand Sanitizer
NDC: 60933-220 | Form: AEROSOL, FOAM
Manufacturer: FULLER INDUSTRIES, INC
Category: otc | Type: HUMAN OTC DRUG LABEL
Date: 20231028

ACTIVE INGREDIENTS: ALCOHOL 620 mg/1 mL
INACTIVE INGREDIENTS: GLYCERETH-2 COCOATE; WATER

Simple Hygiene Foaming Hand Sanitizer

Active ingredient

Ethanol 62%

Purpose

Antiseptic

Uses

- For hand washing to decrease the bacteria on skin.
- Recommended for repeated use

Warnings

For external use only

Flammable, keep away from fire or flame.

Do not use

in the eyes. In case of contact, flush eyes with water.

Stop use and ask a doctor if

- irritation and redness develop
- condition persists for more than 72 hours

Keep out of reach of children.

If swallowed, get medical help or contact a Poison Control Center right away.

DIRECTIONS

- For children under 6, use only under adult supervision
- Pump a small amount of foam into palm of hand
- Wet hands thoroughly with product and allow to dry without wiping

Inactive ingredients

glycereth-2-cocoate, PEG-10 acrylate/perfluorohexyethyl acrylate copolymer/perfluorohexyethyl alcohol, water